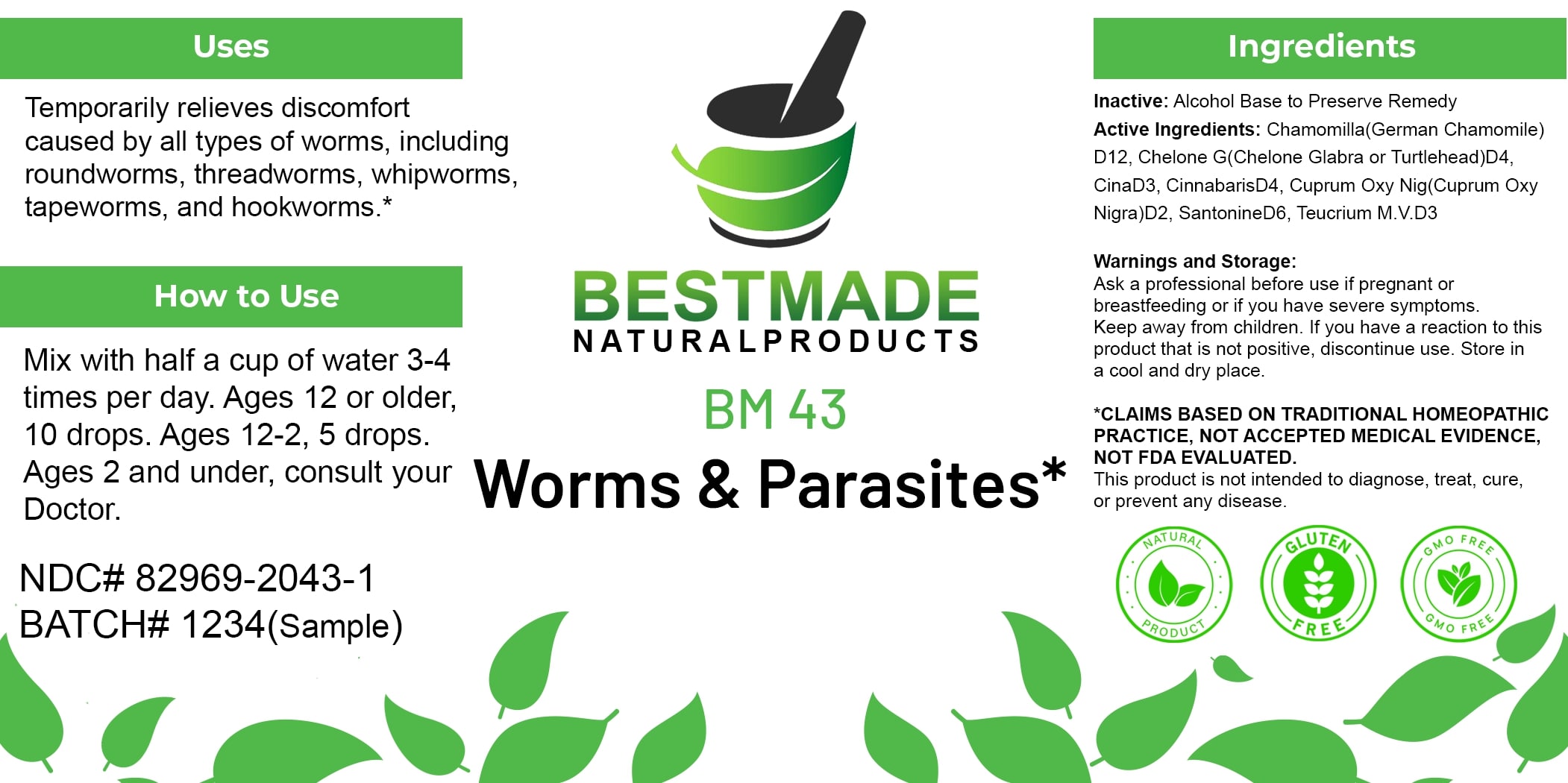 DRUG LABEL: Bestmade Natural Products BM43
NDC: 82969-2043 | Form: LIQUID
Manufacturer: Bestmade Natural Products
Category: homeopathic | Type: HUMAN OTC DRUG LABEL
Date: 20250123

ACTIVE INGREDIENTS: CHAMOMILE 30 [hp_C]/30 [hp_C]; CHELONE GLABRA 30 [hp_C]/30 [hp_C]; ARTEMISIA CINA PRE-FLOWERING TOP 30 [hp_C]/30 [hp_C]; MERCURIC SULFIDE 30 [hp_C]/30 [hp_C]; CUPRIC OXIDE 30 [hp_C]/30 [hp_C]; SANTONIN 30 [hp_C]/30 [hp_C]; TEUCRIUM MARUM 30 [hp_C]/30 [hp_C]
INACTIVE INGREDIENTS: ALCOHOL 30 [hp_C]/30 [hp_C]

BM43

DOSAGE AND ADMINISTRATION

How to Use

Mix with half a cup of water 3-4 times per day. Ages 12 or older, 10 drops. Ages 12-2, 5 drops. Ages 2 and under, consult your Doctor.

INACTIVE INGREDIENT

Ingredients

Inactive: Alcohol Base to Preserve Remedy

Uses

Temporarily relieves discomfort caused by all types of worms, including roundworms, threadworms, whipworms, tapeworms, and hookworms.*

*CLAIMS BASED ON TRADITIONAL HOMEOPATHIC PRACTICE, NOT ACCEPTED MEDICAL EVIDENCE, NOT FDA EVALUATED.

This product is not intended to diagnose, treat, cure, or prevent any disease.

Uses

Temporarily relieves discomfort caused by all types of worms, including roundworms, threadworms, whipworms, tapeworms, and hookworms.*

*CLAIMS BASED ON TRADITIONAL HOMEOPATHIC PRACTICE, NOT ACCEPTED MEDICAL EVIDENCE, NOT FDA EVALUATED.

This product is not intended to diagnose, treat, cure, or prevent any disease.

ACTIVE INGREDIENT

Active Ingredients: Chamomilla (German Chamomile) D12, Chelone G (Chelone Glabra or Turtlehead) D4, Cina D3, Cinnabaris D4, Cuprum Oxy Nig (Cuprum Oxy Nigra) D2, Santonine D6, Teucrium M.V. D3

KEEP OUT OF REACH OF CHILDREN

Warnings and Storage:

Ask a professional before use if pregnant or breastfeeding or if you have severe symptoms. Keep away from children. If you have a reaction to this product that is not positive, discontinue use. Store in a cool and dry place.

Warnings and Storage:

Ask a professional before use if pregnant or breastfeeding or if you have severe symptoms. Keep away from children. If you have a reaction to this product that is not positive, discontinue use. Store in a cool and dry place.

*CLAIMS BASED ON TRADITIONAL HOMEOPATHIC PRACTICE, NOT ACCEPTED MEDICAL EVIDENCE, NOT FDA EVALUATED.

This product is not intended to diagnose, treat, cure, or prevent any disease.

Entire package label